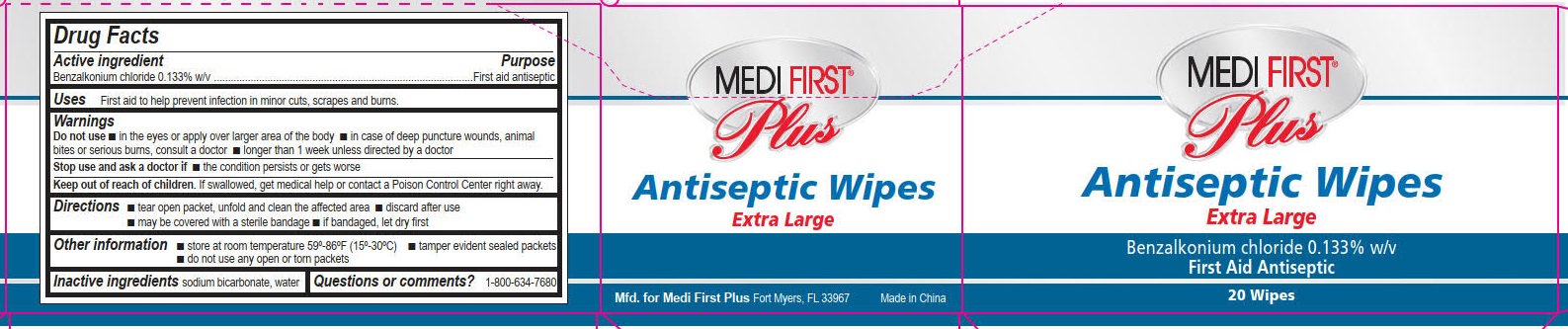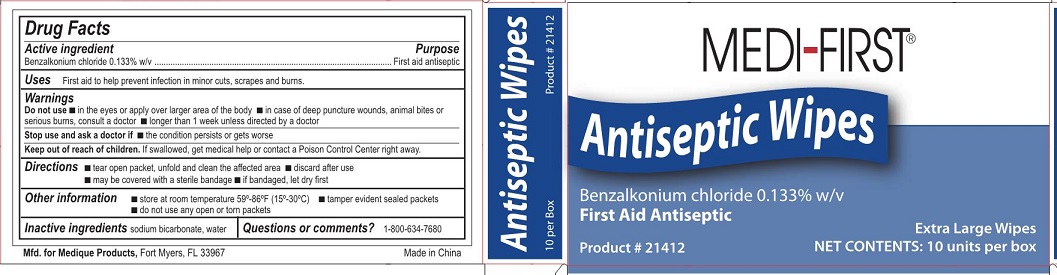 DRUG LABEL: Medi-First Antiseptic Wipes
NDC: 47682-212 | Form: SWAB
Manufacturer: Unifirst First Aid Corporation
Category: otc | Type: HUMAN OTC DRUG LABEL
Date: 20250908

ACTIVE INGREDIENTS: BENZALKONIUM CHLORIDE 1.33 mg/1 mL
INACTIVE INGREDIENTS: SODIUM BICARBONATE; WATER

Unifirst First Aid

Drug Facts

Active ingredient
Benzalkonium chloride 0.133% w/v

Purpose

First aid antiseptic

Uses

First aid to help prevent infection in minor cuts, scrapes, and burns.

Warnings

Do not use

- in the eyes or over large areas of the body
- in case of deep or puncture woulds, animal bite or serious burns, consult a doctor
- longer than 1 week unless directed by a doctor

Stop use and ask a doctor if

- if the condition persists or gets worse

Keep out of reach of children.

If swallowed, get medical help or contact a Poison Control Center right away.

Directions

- tear open packet, unfold and clean the affected area
- discard after use
- may be covered with a sterile bandage
- if bandaged, let dry first

Other information

- store at room temperature 59-86ºF (15-30ºC)
- tamper evident sealed packets
- do not use any open or torn packets

Inactive ingredients

sodium bicarbonate, water

Questions or comments?

1-800-634-7680

Medi-First Antiseptic Wipes Label

Medi-First®

Antiseptic Wipes

Benzalkonium chloride 0.133%

First aid Antiseptic

Product # 21412

Extra Large Wipes

Net Contents: 10 units per box

Medi-First Plus Antiseptic Wipes Label

Medi First ®

Plus

Antiseptic Wipes

Extra Large

Benzalkonium chloride 0.133% w/v

First Aid Antiseptic

Reorder # 103071

20 Wipes